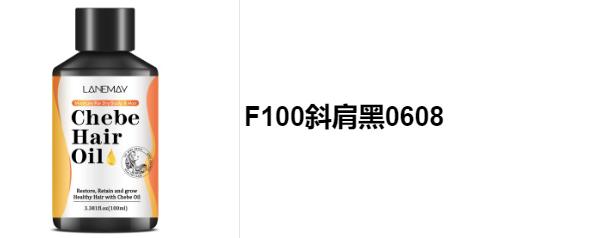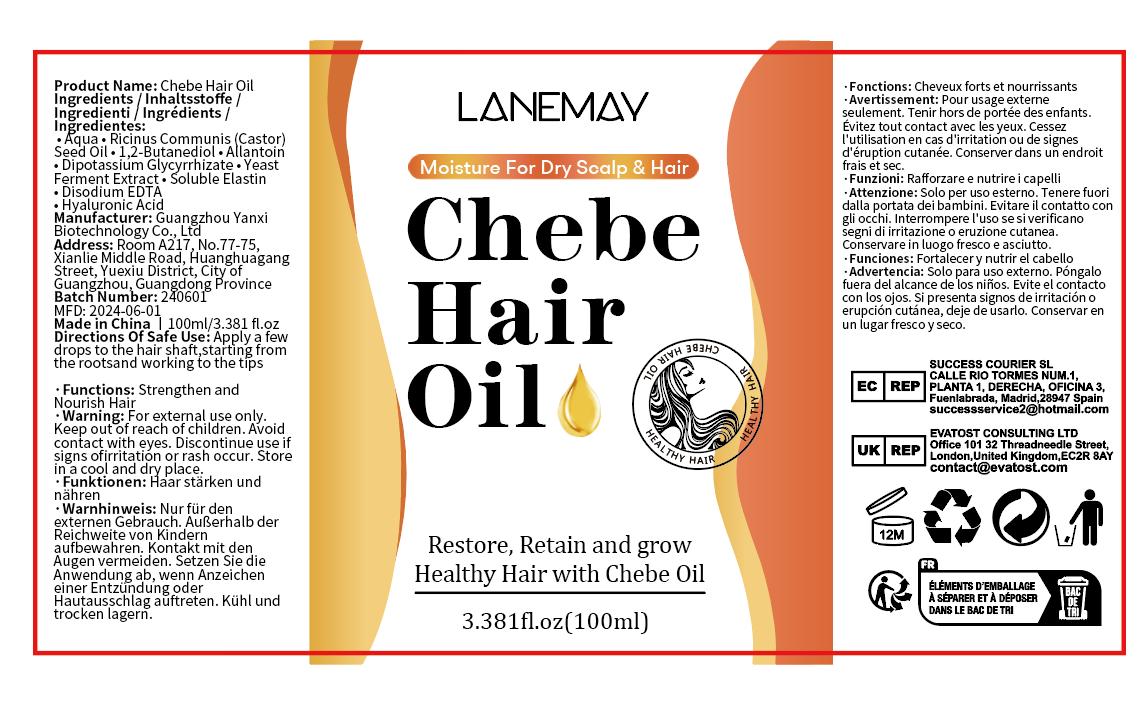 DRUG LABEL: Chebe Hair Oil
NDC: 84025-054 | Form: CREAM
Manufacturer: Guangzhou Yanxi Biotechnology Co., Ltd
Category: otc | Type: HUMAN OTC DRUG LABEL
Date: 20240709

ACTIVE INGREDIENTS: ALLANTOIN 3 mg/100 mL; HYALURONIC ACID 4 mg/100 mL
INACTIVE INGREDIENTS: WATER

DOSAGE AND ADMINISTRATION

use as a normal hair cream

WARNINGS

Keep out of Children

INACTIVE INGREDIENT

Aqua

INDICATIONS AND USAGE

For daily hair care

PURPOSE

Keep out of Children

KEEP OUT OF REACH OF CHILDREN

Strong and nourishing hair